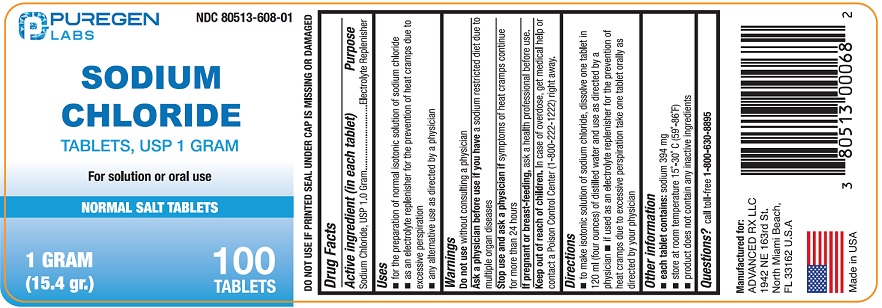 DRUG LABEL: Sodium Chloride

NDC: 80513-608 | Form: TABLET
Manufacturer: Advanced Rx LLC
Category: otc | Type: HUMAN OTC DRUG LABEL
Date: 20250702

ACTIVE INGREDIENTS: SODIUM CHLORIDE 1 g/1 1

Sodium Chloride Tablets, USP

Drug Facts

Active ingredient (in each tablet)

Sodium Chloride, USP 1.0 Gram

Purpose

Electrolyte Replenisher

Uses

- for the preparation of normal isotonic solution of sodium chloride
- as an electrolyte replenisher for the prevention of heat cramps due to excessive perspiration
- any alternative use as directed by a physician

Warnings

Do not usewithout consulting a physician

ASK DOCTOR

Ask a physician before use if you havea sodium restricted diet due to multiple organ diseases

Stop use and ask a physician ifsymptoms of heat cramps continue for more than 24 hours.

PREGNANCY OR BREAST FEEDING

If pregnant or breast-feeding,ask a health professional before use.

Keep out of reach of children.

In case of overdose, get medical help or contact a Poison Control Center (1-800-222-1222) right away.

Directions

- to make isontonic solution of sodium chloride, dissolve one tablet in 120 ml (four ounces) of distilled water and use as directed by a physician.
- if used as an electrolyte replenisher for the prevention of heat cramps due to excessive perspiration take one tablet orally as directed by your physician.

Other information

- each tablet contains:sodium 394 mg
- store at room temperature 15°-30°C (59°-86°F)
- product does not contain any inactive ingredients
- DO NOT USE IF PRINTED SAFETY SEAL UNDER CAP IS MISSING OR DAMAGED

INACTIVE INGREDIENT

None

Questions?

call toll-free 1-800-630-8895

Manufactured for:

Advanced Rx LLC

1942 NE 163rd St.

North Miami Beach,

FL 33162 U.S.A.

Made in USA

PACKAGE LABEL

NDC 80513-608-01

Sodium Chloride Tablets, USP 1 Gram

Normal Salt Tablets

For solution or oral use

100 Tablets